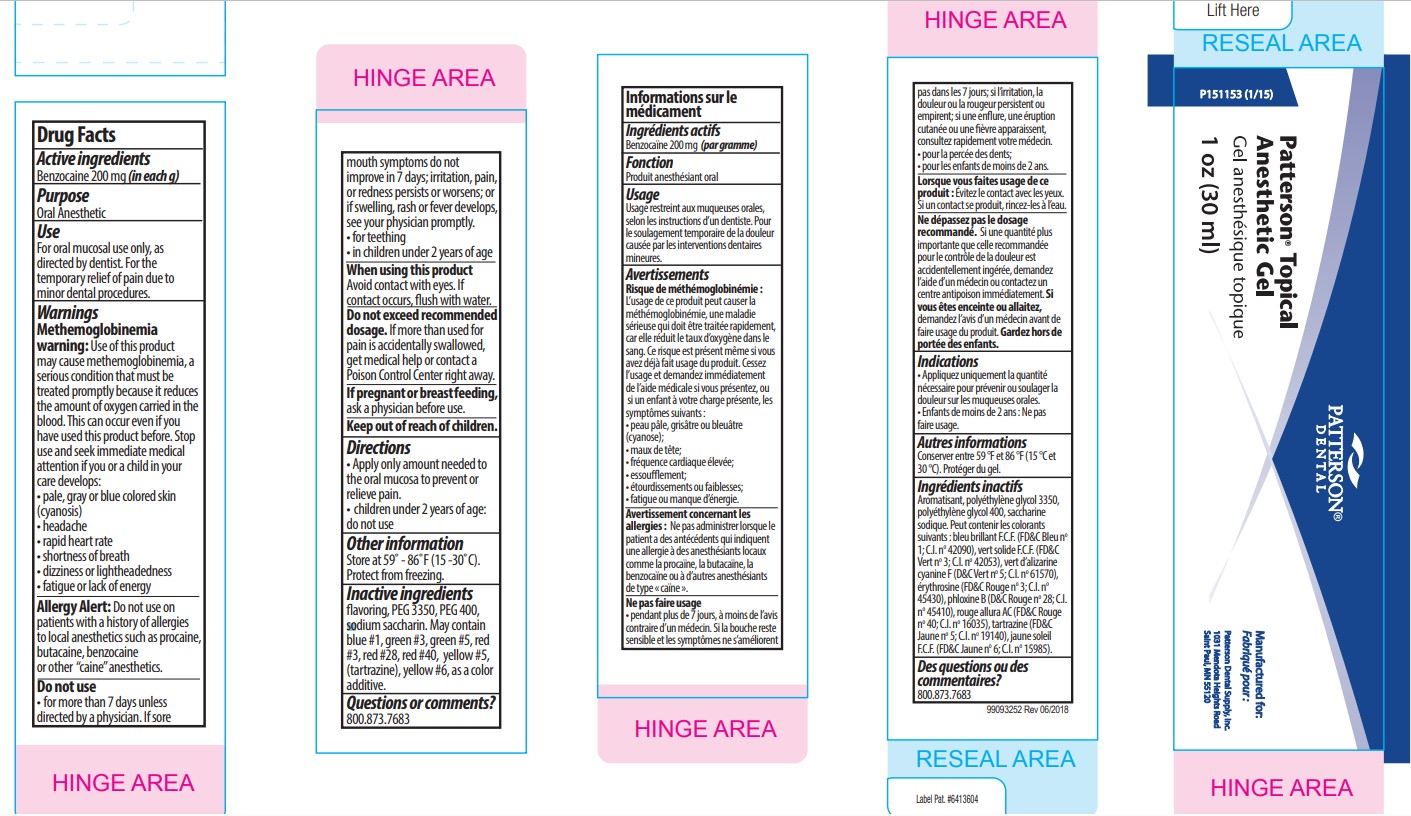 DRUG LABEL: Patterson Dental Topical Anesthetic
NDC: 50227-1013 | Form: GEL
Manufacturer: Patterson Dental
Category: otc | Type: HUMAN OTC DRUG LABEL
Date: 20250918

ACTIVE INGREDIENTS: BENZOCAINE 200 mg/1 g
INACTIVE INGREDIENTS: POLYETHYLENE GLYCOL 3350; SACCHARIN SODIUM; POLYETHYLENE GLYCOL 400

ACTIVE INGREDIENT

Benzocaine 200mg (in each g)

PURPOSE

Oral Anesthetic

INDICATIONS AND USAGE

For oral mucosal use only, as directed by dentist. For the temporary relief of pain due to minor dental procedures.

WARNINGS

Methemoglobinemia warning: Use of this product may cause methemoglobinemia, a serious condition that must be treated promptly because it reduces the amount of o product before. Stop use and seek immediate medical attention if you or a child in your care develops:

- pale, gray or blue colored skin (cyanosis)
- headache
- rapid heart rate
- shortness of breath
- dizziness or lightheadedness
- fatigue or lack of energy

Allergy Alert: Do not use on patients with a history of allergies to local anesthetics such as procaine, butacaine, benzocaine or other "caine" anesthetics.

Do not use

- for more than 7 days unless directed by a physician. If sore mouth symptoms do not improve in 7 days; irritation, pain, or redness persists or worsens; or if swelling, rash or fever develops, see your physician promptly.
- for teething
- in children under 2 years of age

When using this product Avoid contact with eyes. If contact occurs, flush with water.

Do not exceed recommended dosage. If more than used for pain is accidentally swallowed, get medical help or contact a Poison Control Center right away.

If pregnant or breast feeding, ask a physician before use.

DOSAGE AND ADMINISTRATION

- Apply only amount needed to the oral mucosa to prevent or relieve pain.
- children under 2 years of age: do not use

Keep out of reach of children.

STORAGE AND HANDLING

Store at 59°-86°F (15°-30°C). Protect from freezing.

INACTIVE INGREDIENT

flavoring, PEG 3350, PEG 400, sodium saccharin. May contain blue #1, green #3, green #5, red #3, red #28, red #40, yellow #5, (tartrazine), yellow #6, as a color additive.

QUESTIONS

800.873.7683